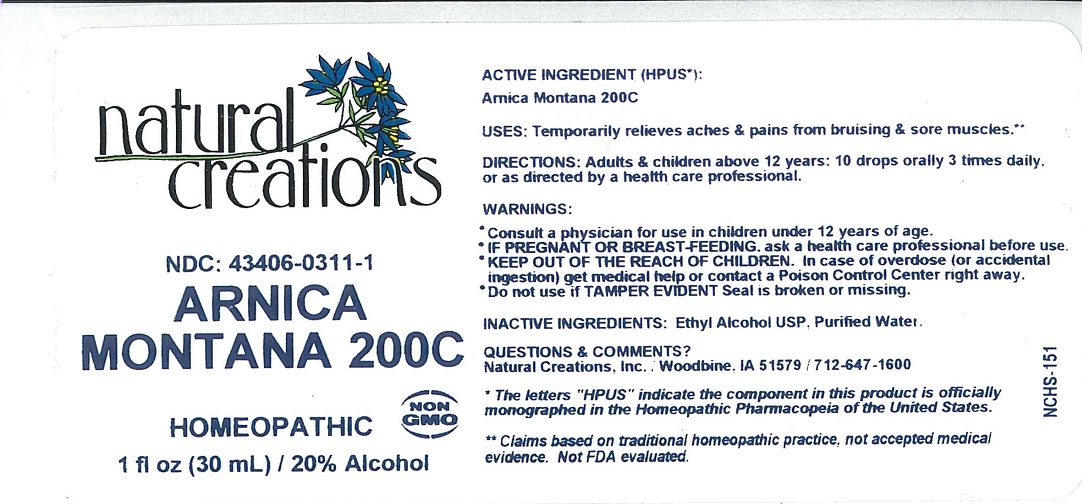 DRUG LABEL: ARNICA MONTANA 200C
NDC: 43406-0311 | Form: LIQUID
Manufacturer: Natural Creations, Inc.
Category: homeopathic | Type: HUMAN OTC DRUG LABEL
Date: 20220217

ACTIVE INGREDIENTS: ARNICA MONTANA 200 [hp_C]/1 mL
INACTIVE INGREDIENTS: ALCOHOL; WATER

ARNICA MONTANA 200C

ACTIVE INGREDIENT (HPUS*):

Arnica Montana 200C

PURPOSE

USES: Temporarily relieves aches & pains from bruising & sore muscles.**

INDICATIONS AND USAGE

USES: Temporarily relieves aches & pains from bruising & sore muscles.**

DOSAGE AND ADMINISTRATION

DIRECTIONS: Adults & children above 12 years: 10 drops orally 3 times daily, or as directed by a health care professional.

WARNINGS:

- Consult a physician for use in children under 12 years of age.

- IF PREGNANT OR BREAST-FEEDING, ask a health care professional before use.

- KEEP OUT OF HTE REACH OF CHILDREN. In case of overdose (or accidental ingestion) get medical help or contact a Poison Control Center right away.

- Do not use if TAMPER EVIDENT Seal is broken or missing.

WARNINGS:

- Consult a physician for use in children under 12 years of age.

- IF PREGNANT OR BREAST-FEEDING, ask a health care professional before use.

- KEEP OUT OF HTE REACH OF CHILDREN. In case of overdose (or accidental ingestion) get medical help or contact a Poison Control Center right away.

- Do not use if TAMPER EVIDENT Seal is broken or missing.

INACTIVE INGREDIENTS: Ethyl Alcohol USP, Purified Water.

QUESTIONS & COMMENTS?

Natural Creations, Inc. / Woodbine, IA 51579 / 712-647-1600

REFERENCES

* The letters "HPUS" indicate the component in this product is officially monographed in the Homeopathic Pharmacopeia of the United States.

** Claims based on traditional homeopathic practice, not accepted medical evidence. Not FDA evaluated.

PACKAGE LABEL

NDC: 43406-0311-1

ARNICA

MONTANA 200C

HOMEOPATHIC

1 fl oz (30 mL) / 20% Alcohol